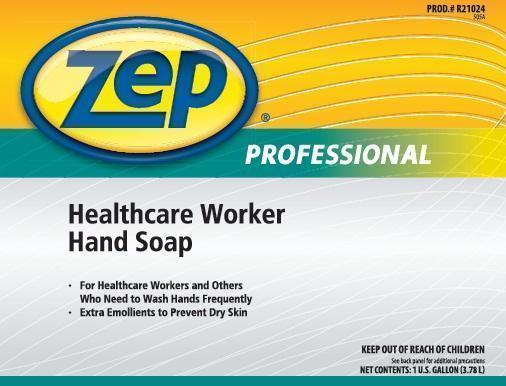 DRUG LABEL: Zep Professional Healthcare Worker
NDC: 66949-210 | Form: LIQUID
Manufacturer: Zep Inc.
Category: otc | Type: HUMAN OTC DRUG LABEL
Date: 20131205

ACTIVE INGREDIENTS: TRICLOSAN .01 g/10 mL
INACTIVE INGREDIENTS: WATER; SODIUM LAURYL SULFOACETATE; DISODIUM LAURETH SULFOSUCCINATE; SODIUM COCOYL SARCOSINATE; COCAMIDOPROPYL PG-DIMONIUM CHLORIDE PHOSPHATE; GLYCERIN; HEXYLENE GLYCOL; PEG-75 LANOLIN; METHYLCHLOROISOTHIAZOLINONE; METHYLISOTHIAZOLINONE; GLUTARAL

Zep Professional Healthcare Worker Hand Soap

Active ingredient

Triclosan 0.1%

Purpose

Antimicrobial

Uses

Hand washing to decrease bacteria on skin.

Warnings

For external use only.

Do not use in the eyes.

When using this product

- If swallowed, seek medical attention.
- If eye contact occurs, flush eyes with water and contact a physician.
- Discontinue use if irritation and redness develop.
- If condition persists for more than 72 hours, consult a doctor.

Keep out of reach of children.

Directions

- Wet hands with water
- Place hands under dispenser
- Apply foamed soap
- Massage soap into hands and wrists, emphasizing back of hands, knuckles and cuticles
- Rinse thoroughly

Other information

- Store at room temperature.
- Do not freeze.

Inactive ingredients

Water, Sodium Lauryl Sulfoacetate (and) Disodium Laurethsulfosuccinate, Sodium Cocoyl Sarcosinate, Cocamidopropyl PG-Dimonium Chloride Phosphate, Glycerine, Hexylene Glycol, PEG-75 Lanolin, Tetrasodium EDTA, Methylchloroisothiazolinone (and) Methylisothiazoline, Fragrance, Glutaral